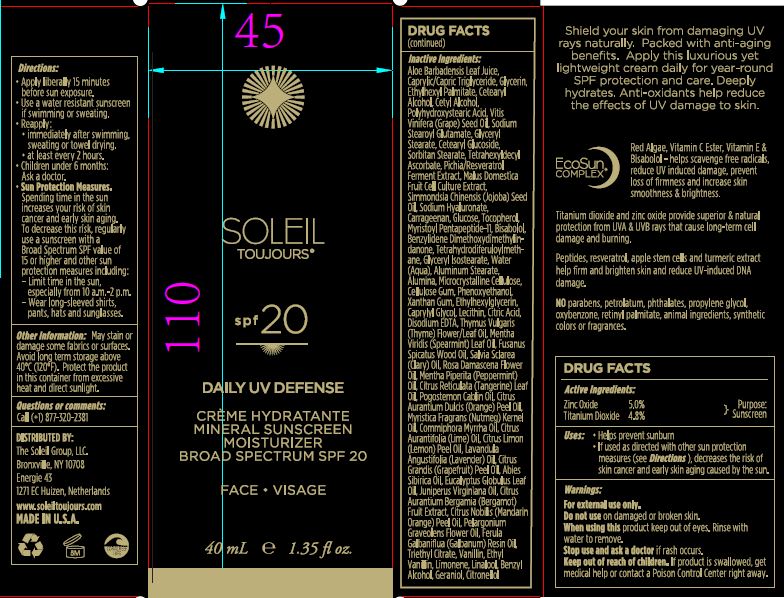 DRUG LABEL: Mineral Sunscreen Moisturizer Broad Spectrum SPF 20
NDC: 62742-4153 | Form: CREAM
Manufacturer: Allure Labs, Inc
Category: otc | Type: HUMAN OTC DRUG LABEL
Date: 20171212

ACTIVE INGREDIENTS: ZINC OXIDE 50.0 mg/1 mL; TITANIUM DIOXIDE 48.0 mg/1 mL
INACTIVE INGREDIENTS: ALOE; MEDIUM-CHAIN TRIGLYCERIDES; GLYCERIN; ETHYLHEXYL PALMITATE; CETYL ALCOHOL; CETOSTEARYL ALCOHOL; POLYHYDROXYSTEARIC ACID (2300 MW); VITIS VINIFERA SEED; SODIUM STEAROYL GLUTAMATE; GLYCERYL STEARATE SE; CETEARYL GLUCOSIDE; SORBITAN MONOSTEARATE; TETRAHEXYLDECYL ASCORBATE; MALUS DOMESTICA FLOWER; SIMMONDSIA CHINENSIS SEED; HYALURONATE SODIUM; CARRAGEENAN; DEXTROSE, UNSPECIFIED FORM; TOCOPHEROL; .ALPHA.-BISABOLOL, (+/-)-; BENZYLIDENE DIMETHOXYDIMETHYLINDANONE; TETRAHYDRODIFERULOYLMETHANE; GLYCERYL ISOSTEARATE; WATER; ALUMINUM STEARATE; ALUMINUM OXIDE; MICROCRYSTALLINE CELLULOSE; CARBOXYMETHYLCELLULOSE SODIUM, UNSPECIFIED FORM; PHENOXYETHANOL; XANTHAN GUM; ETHYLHEXYLGLYCERIN; CAPRYLYL GLYCOL; LECITHIN, SOYBEAN; CITRIC ACID MONOHYDRATE; EDETATE DISODIUM; THYMUS VULGARIS LEAF; SPEARMINT OIL; SANTALUM SPICATUM OIL; ROSA DAMASCENA FLOWER OIL; PEPPERMINT OIL; CITRUS RETICULATA LEAF OIL; PATCHOULI OIL; ORANGE PEEL; NUTMEG OIL; MYRRH OIL; LIME OIL; LEMON OIL; LAVENDER OIL; GRAPEFRUIT PEEL; ABIES SIBIRICA LEAF OIL; EUCALYPTUS GLOBULUS LEAF; JUNIPERUS VIRGINIANA OIL; BERGAMOT OIL; MANDARIN OIL; GALBANUM OIL; TRIETHYL CITRATE; VANILLIN; ETHYL VANILLIN; LIMONENE OXIDE, (+)-; LINALOOL, (+)-; BENZYL ALCOHOL; GERANIOL; CITRONELLOL ACETATE, (R)-

Drug Facts

ACTIVE INGREDIENT

Titanium Dioxide - 4.80%

Zinc Oxide - 5.00%

INDICATIONS AND USAGE

Helps prevent sunburn

if used as directed with other sun protection measures, decreases the risk of skin cancer and early skin aging caused by the sun.

WARNINGS

For external use only.

do not use on damaged or broken skin.

When using this product keep out of eyes. Rinse with water to remove.

Stop use and ask a doctor if rash occurs.

KEEP OUT OF REACH OF CHILDREN

if product is swallowed, get medical help or contact a Poison Control Center right away.

DOSAGE AND ADMINISTRATION

apply liberally 15 minutes before sun exposure.

use a water resistant sunscreen if swimming or sweating.

reapply:

immidiately aftr swimming, sweating or towel drying.

at least every 2 hours.

children under 6months: ask doctor

Sun protection measures:

Spending time in the sun increases your risk of skin cancer and early skin aging. To decrease the risk, regularly use a sunscreen with a Broad Spectrum SPF value of 15 or higher and other sun protector measures including:

limit time in the sun, especially from 10:00 am to 2:00 pm.

wear long sleaved shirts, pants, hats and sun glasses.

OTHER SAFETY INFORMATION

May stain or damage some fabrics or surfaces. Avoid long term storage above 40C (120F). Protect the product in this container from excessive heat and direct sunlight.

INACTIVE INGREDIENT

Aloe Barbadensis Leaf Juice, Caprylic/Capric Triglyceride, Ethylhexyl Palmitate, Glycerin, Cetearyl Alcohol, Cetyl Alcohol, Polyhydroxysteari Acid, Vitis Vinifera (Grape) Seed Oil, Sodium Stearoyl Glutamate, Glyceryl Stearate, Cetearyl Glucoside, Sorbitan Stearate, Tetrahexyldecyl Ascorbate, Pichia/Resveratrol Ferment Extract, Malus Domestica Fruit Cell Culture Extract, Simmondsia Chinesis (Jojoba) Seed Oil, Sodium Hyaluronate, Carrageenan, Glucose, Tocopherol, Myristoyl Pentapeptide-11, Bisabolol, Benzylidene Dimethoxydimethylindanone, Tetrahydrodiferuloylmethane, Glyceryl Isostearate, Water (Aqua), Aluminum Stearate, Alumina, Microcrystalline Cellulose, Cellulose Gum, Phenoxyethanol, Xanthan Gum, Ethylhexylglycerin, Caprylyl Glycol, Lecithin, Citric Acid, Disodium EDTA, Thymus Vulgaris (Thyme) Flower/Leaf Oil, Mentha Viridis (Spearmint) Leaf Oil, Fusanus Spicatus Wood Oil, Salvia Sclarea (Clary) Oil, Rosa Damascena Flower Oil, Mentha Piperita (Peppermint) Oil, Citrus Reticulata (Tangerine) Leaf Oil, Pogostemon Cablin Oil, Citrus Aurantium Dulcis (Orange) Peel Oil, Myristica Fragrans (Nutmeg) Kernel Oil, Commiphora Myrrha Oil, Citrus Aurantifolia (Lime) Oil, Citrus Limon (Lemon) Peel Oil, Lavandula Angustifolia (Lavender) Oil, Citrus Grandis (Grapefruit) Peel Oil, Abies Sibirica Oil, Eucalyptus Globulus Leaf Oil, Juniperus Virginiana Oil, Citrus Aurantium Bergamia (Bergamot) Fruit Extract, Citrus Nobilis (Mandarin Orange) Peel Oil, Pelargonium Graveolens Flower Oil, Ferula Galbaniflua (Galbanum) Resin Oil, Triethyl Citrate, Vanillin, Ethyl Vanillin, Limonene, Linalool, Benzyl Alcohol, Feraniol, Citronellol.

PACKAGE LABEL

Distributed By:

The Soleil Group, LLC.

Bronxville, NY 10708

Energie 43

1271 EC Huizen, Netherlands

www.soleiltoujours.com

MADE IN U.S.A.